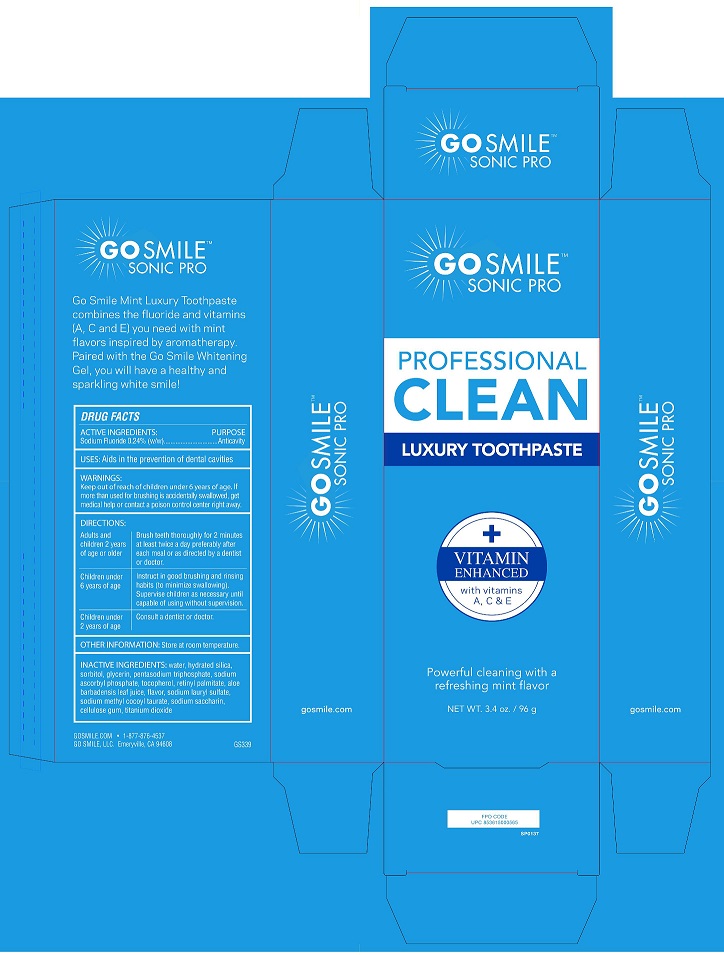 DRUG LABEL: Go Smile
NDC: 44873-008 | Form: PASTE, DENTIFRICE
Manufacturer: Go Smile, Inc.
Category: otc | Type: HUMAN OTC DRUG LABEL
Date: 20231115

ACTIVE INGREDIENTS: SODIUM MONOFLUOROPHOSPHATE 0.76 g/100 g
INACTIVE INGREDIENTS: SORBITOL; WATER; HYDRATED SILICA; GLYCERIN; SODIUM LAURYL SULFATE; CARBOXYMETHYLCELLULOSE SODIUM; TITANIUM DIOXIDE; SODIUM BENZOATE; SACCHARIN SODIUM; VALERIAN

GOSMILE (as PLD) - TOOTHPASTE, MINT (44873-008)

PURPOSE

ANTICAVITY

KEEP OUT OF REACH OF CHILDREN UNDER 6 YEARS OLD.

DIRECTIONS

Adults and children 2 years of age or older – Brush teeth thoroughly for 2 minutes at least twice a day preferably after each meal or as directed by a dentist or doctor.
Children under 6 years of age – Instruct in good brushing and rinsing habits (to minimize swallowing). Supervise children as necessary until capable of using without supervision.
Children under 2 years of age – Consult a dentist or doctor

INACTIVE INGREDIENTS

Water, hydrated silica, sorbitol, glycerin, pentasodium triphosphate, sodium ascorbyl phosphate, tocopherol, retinyl palmitate, aloe barbadensis leaf juice, flavor, sodium lauryl sulfate, sodium methyl cocoyl taurate, sodium saccharin, cellulose gum, titanium dioxide

USES

Aids in the prevention of dental cavities

ACTIVE INGREDIENTS

Sodium Fluoride 0.24% (w/w)

WARNINGS

If more than used for brushing is accidentally swallowed, get medical help or contact a poison control center right away.

OTHER INFORMATION

STORE AT ROOM TEMPERATURE.